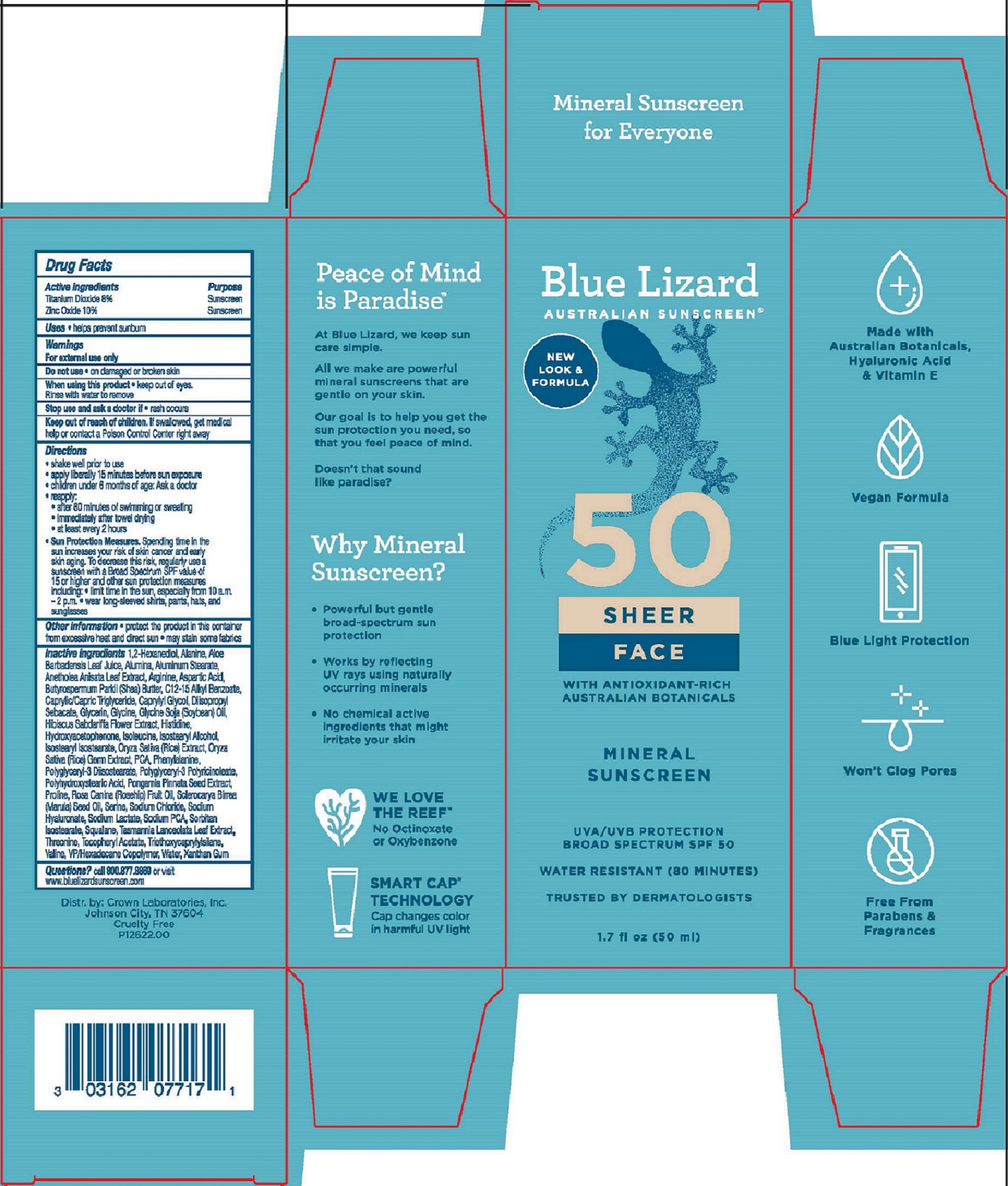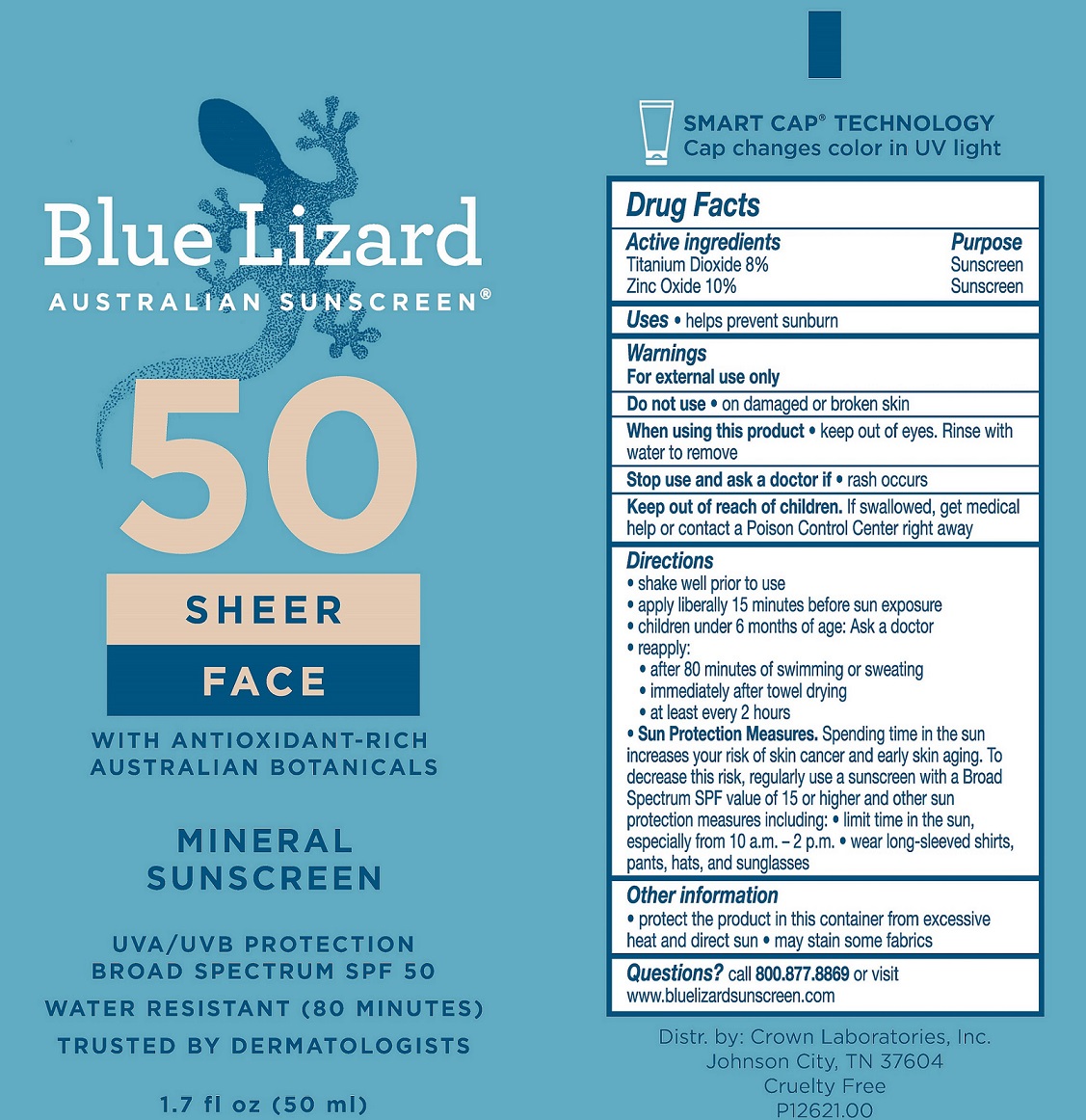 DRUG LABEL: Blue Lizard Sheer Face SPF 50 Sunscreen
NDC: 0316-2077 | Form: LOTION
Manufacturer: Crown Laboratories
Category: otc | Type: HUMAN OTC DRUG LABEL
Date: 20260112

ACTIVE INGREDIENTS: TITANIUM DIOXIDE 91.2 mg/1 mL; ZINC OXIDE 114 mg/1 mL
INACTIVE INGREDIENTS: BUTYROSPERMUM PARKII (SHEA) BUTTER; ISOSTEARYL ALCOHOL; RICE GERM; POLYGLYCERYL-3 DIISOSTEARATE; ISOLEUCINE; PONGAMIA PINNATA SEED; SCLEROCARYA BIRREA SEED OIL; SODIUM LACTATE; VALINE; TASMANNIA LANCEOLATA LEAF; ALANINE; ARGININE; SOYBEAN OIL; HYALURONATE SODIUM; HISTIDINE; HYDROXYACETOPHENONE; PCA; ASPARTIC ACID; CAPRYLYL GLYCOL; DIISOPROPYL SEBACATE; ROSA CANINA FRUIT OIL; SQUALANE; SYZYGIUM ANISATUM LEAF; HIBISCUS SABDARIFFA FLOWER; 1,2-HEXANEDIOL; SODIUM CHLORIDE; ALOE BARBADENSIS LEAF JUICE; SORBITAN ISOSTEARATE; POLYGLYCERYL-3 PENTARICINOLEATE; PROLINE; ISOSTEARYL ISOSTEARATE; PHENYLALANINE; ALUMINUM STEARATE; ALUMINUM OXIDE; TRIETHOXYCAPRYLYLSILANE; ALKYL (C12-15) BENZOATE; WATER; .ALPHA.-TOCOPHEROL ACETATE; HEXADECYL POVIDONE (4 HEXADECYL BRANCHES/REPEAT); POLYHYDROXYSTEARIC ACID (2300 MW); THREONINE; XANTHAN GUM; SERINE; GLYCINE; CAPRYLIC/CAPRIC TRIGLYCERIDE; GLYCERIN; SODIUM PCA

Blue Lizard Sheer Face SPF 50 Sunscreen

Active ingredients

Titanium Dioxide 8%

Zinc Oxide 10%

Purpose

Sunscreen

Uses

- helps prevent sunburn

Warnings

For external use only

Do not use • on damaged or broken skin

When using this product • keep out of eyes. Rinse with water to remove

Stop use and ask doctor if • rash occurs

Keep out of reach of children. If swallowed, get medical help or contact a Poison Control Center right away

Directions

• shake well prior to use

• apply liberally 15 minutes before sun exposure

• children under 6 months of age: ask a doctor

• reapply: • after 80 minutes of swimming or sweating • immediately after towel drying • at least every 2 hours

• Sun Protection Measures. Spending time in the sun increases your risk of skin cancer and early skin aging. To decrease this risk, regularly use a sunscreen with a Broad Spectrum SPF value of 15 or higher and other sun protection measures including: • limit time in the sun, especially from 10 a.m. - 2 p.m. • wear long-sleeved shirts, pants, hats, and sunglasses.

Other information

- protect the product in this container from excessive heat and direct sun
- may stain some fabrics

Inactive ingredients

1,2-Hexanediol, Alanine, Aloe Barbadensis Leaf Juice, Alumina, Aluminum Stearate, Anetholea Anisata Leaf Extract, Arginine, Aspartic Acid, Butyrospermum Parkii (Shea) Butter, C12-15 Alkyl Benzoate, Caprylic/Capric Triglyceride, Caprylyl Glycol, Diisopropyl Sebacate, Glycerin, Glycine, Glycine Soja (Soybean) Oil, Hibiscus Sabdariffa Flower Extract, Histidine, Hydroxyacetophenone, Isoleucine, Isostearyl Alcohol, Isostearyl Isostearate, Oryza Sativa (Rice) Extract, Oryza Sativa (Rice) Germ Extract, PCA, Phenylalanine, Polyglyceryl-3 Diisostearate, Polyglyceryl-3 Polyricinoleate, Polyhydroxystearic Acid, Pongamia Pinnata Seed Extract, Proline, Rosa Canina (Rosehip) Fruit Oil, Sclerocarya Birrea (Marula) Seed Oil, Serine, Sodium Chloride, Sodium Hyaluronate, Sodium Lactate, Sodium PCA, Sorbitan Isostearate, Squalane, Tasmannia Lanceolata Leaf Extract, Threonine, Tocopheryl Acetate, Triethoxycaprylylsilane, Valine, VP/Hexadecane Copolymer, Water, Xanthan Gum

Questions?

call 800.877.8869 or visit www.bluelizardsunscreen.com

Blue Lizard Sheer Face 1.7 oz Tube

Blue Lizard

Australian Sunscreen

50

SHEER
FACE

with Antioxidant-Rich

Australian Botanicals

MINERAL

SUNSCREEN

UVA/UVB PROTECTION

BROAD SPECTRUM SPF 50

WATER RESISTANT (80 MINUTES)

TRUSTED BY DERMATOLOGISTS

1.7 fl oz (50 ml)

Blue Lizard Sheer Face 1.7 oz Carton

Blue Lizard

Australian Sunscreen

50

SHEER
FACE

with Antioxidant-Rich

Australian Botanicals

MINERAL

SUNSCREEN

UVA/UVB PROTECTION

BROAD SPECTRUM SPF 50

WATER RESISTANT (80 MINUTES)

TRUSTED BY DERMATOLOGISTS

1.7 fl oz (50 ml)